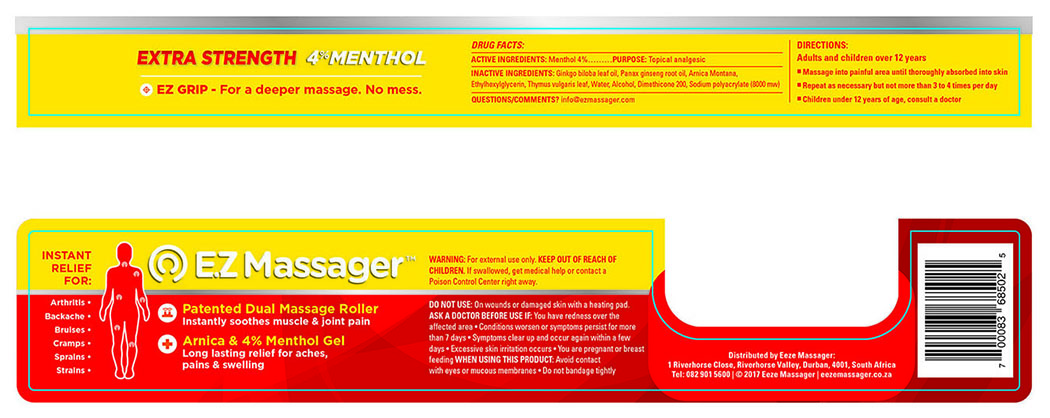 DRUG LABEL: Ez Massager 4
NDC: 71633-004 | Form: GEL
Manufacturer: CunningPac
Category: otc | Type: HUMAN OTC DRUG LABEL
Date: 20170823

ACTIVE INGREDIENTS: MENTHOL 2 g/100 mL
INACTIVE INGREDIENTS: GINKGO BILOBA LEAF OIL; SODIUM POLYACRYLATE (8000 MW); WATER; ALCOHOL; DIMETHICONE 200; ARNICA MONTANA; ETHYLHEXYLGLYCERIN; PANAX GINSENG ROOT OIL; THYMUS VULGARIS LEAF

DOSAGE AND ADMINISTRATION

Massage into painful area until thoroughly absorbed into skin

repeat as necessary but not more than 3 to 4 times per day

WARNINGS

WARNING: For external use only

DO NOT USE: On wounds or damaged skin with a heating pad

ASK A DOCTOR BEFORE USE IF:

* You have redness over the affected area

* Conditions Worsen or symptoms persisist for more than 7 days

* Symptoms clear up and occur again within a few days

* Excessive skin irratation occurs

* You are pregnant or breast feeding

INACTIVE INGREDIENT

GINKGO BILOBA LEAF OIL

PANAX GINSENG ROOT OIL

ARNICA MONTANA

THYMUS VULGARIS LEAF

WATER

ALCOHOL

SODIUM POLYACRYLATE (8000 MW)

DIMETHICONE 200

ETHYLHEXYLGLYCERIN

INDICATIONS AND USAGE

Instant relief for:

Arthritis

Backache

Bruises

Cramps

Sprains

Strains

WHEN USING THIS PRODUCT:

* Avoid contact with eyes or micous membranes

* Do not bandage tightly

PURPOSE

Topical Analgesic

KEEP OUT OF REACH OF CHILDREN: If swallowed, get medical help or contact a Poisen Control Center right away.

ACTIVE INGREDIENT

Menthol 2 %